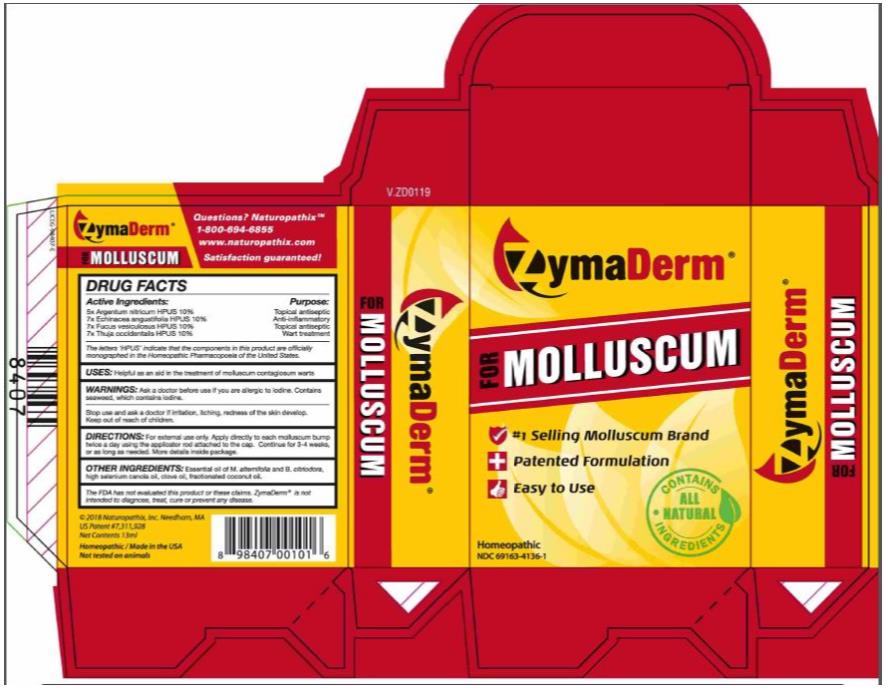 DRUG LABEL: ZymaDerm
NDC: 69163-4136 | Form: LIQUID
Manufacturer: Naturopathix, Inc.
Category: homeopathic | Type: HUMAN OTC DRUG LABEL
Date: 20210115

ACTIVE INGREDIENTS: SILVER NITRATE 5 [hp_X]/13 mL; ECHINACEA ANGUSTIFOLIA 7 [hp_C]/13 mL; FUCUS VESICULOSUS 7 [hp_X]/13 mL; THUJA OCCIDENTALIS LEAFY TWIG 7 [hp_X]/13 mL
INACTIVE INGREDIENTS: TEA TREE OIL; BACKHOUSIA CITRIODORA WHOLE; CANOLA OIL; CLOVE OIL; COCONUT OIL

Zymaderma For Molluscum

ZymaDerm® for Molluscum - Drug Facts

Active Ingredients:

5x Argentum nitricum HPUS 10%

7x Echinacea agustifolia HPUS 10%

7x Fucus vesiculosus HPUS 10%

7x Thuja occidentalis HPUS 10%

Purpose:

Topical antiseptic

Anti-inflammatory

Topical antiseptic

Wart treatment

The letters ‘HPUS’ indicate that the components in this product are officially monographed in the Homeopathic Pharmacopoeia of the United States

Uses:

Helpful as an aid in the treatment of molluscum contagiosum warts

Warnings:

Ask a doctor before use if you are allergic to iodine. Contains seaweed, which contains iodine.

Stop use and ask a doctor

if irritation, itching, redness of the skin develop.

Directions:

For external use only. Apply directly to each molluscum bump twice a day using the applicator rod attached to the cap. Continue for 3-4 weeks, or as long as needed. More details inside package.

Other Ingredients:

Essential oil of M. alternifolia and B. citriodora, high selenium canola oil, clove oil, fractionated coconut oil.

The FDA has not evaluated this product or these claims. ZymaDerm™ is not intended to diagnose, treat, cure or prevent any disease.

PRINCIPAL DISPLAY PANEL

NDC 69163-4136-1
ZymaDerm
FOR MOLLUSCUM
Homeopathic